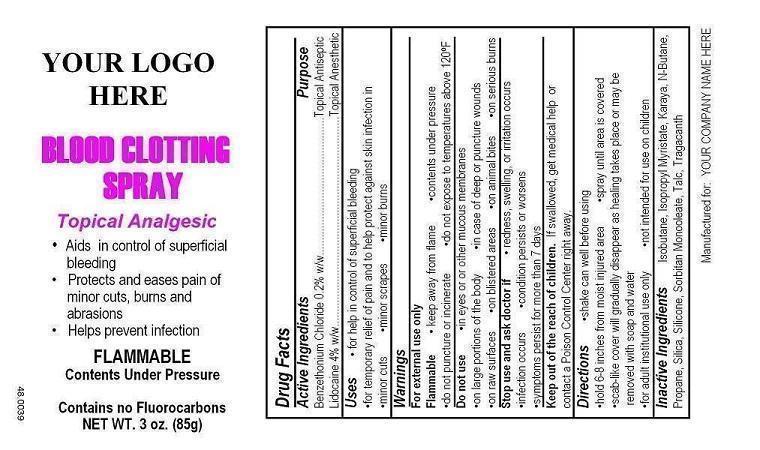 DRUG LABEL: Your Label Here Blood Clotting First Aid
NDC: 52982-106 | Form: AEROSOL, SPRAY
Manufacturer: Dixon Investments, Inc.
Category: otc | Type: HUMAN OTC DRUG LABEL
Date: 20250128

ACTIVE INGREDIENTS: LIDOCAINE 3400 mg/85 g; BENZETHONIUM CHLORIDE 170 mg/85 g
INACTIVE INGREDIENTS: ISOBUTANE; ISOPROPYL MYRISTATE; KARAYA GUM; BUTANE; PROPANE; SILICON DIOXIDE; 3-(TRIETHOXYSILYL)PROPYLAMINE; SORBITAN MONOOLEATE; TALC; TRAGACANTH

YOUR LOGO HERE BLOOD CLOTTING SPRAY

Active Ingredients

Benzethonium Chloride 0.2% w/w
Lidocaine 4% w/w

Purpose

Topical Antiseptic
Topical Anesthetic

Uses

for help in control of superficial bleeding
for temporary relief of pain and to help protect against skin infestion in minor cuts
minor cuts
minor scrapes
minor burns

Warnings

For external use only

Flammable

keep away from flame
contents under pressure
do not puncture or incinerate
do not expose to temperatures above 120°(F)

Do not use

in eyes or other mucous membranes
on large portions of the body
in case of deep or puncture wounds
on raw surfaces
on blistered areas
on animal bites
on serious burns

Stop use and ask doctor if

redness, swelling, or irritation occurs
infection occurs
condition persists or worsens
symptoms persist for more than 7 days

Keep out of reach of children.

If swallowed, get medical help or contact a Poison Control Center right away.

Directions

shake can well before using
hold 6-8 inches from moist injured area
spray until area is covered
scan-like cover will gradually disappear as healing takes place or may be removed with soap and water
for adult institutional use only
not intended for use on children

Inactive Ingredients

Isobutane, Isopropyl Myristate, Karaya, N-Butane, Propane, Silica, Silicone, Sorbitan Monooleate, Talc, Tragacanth